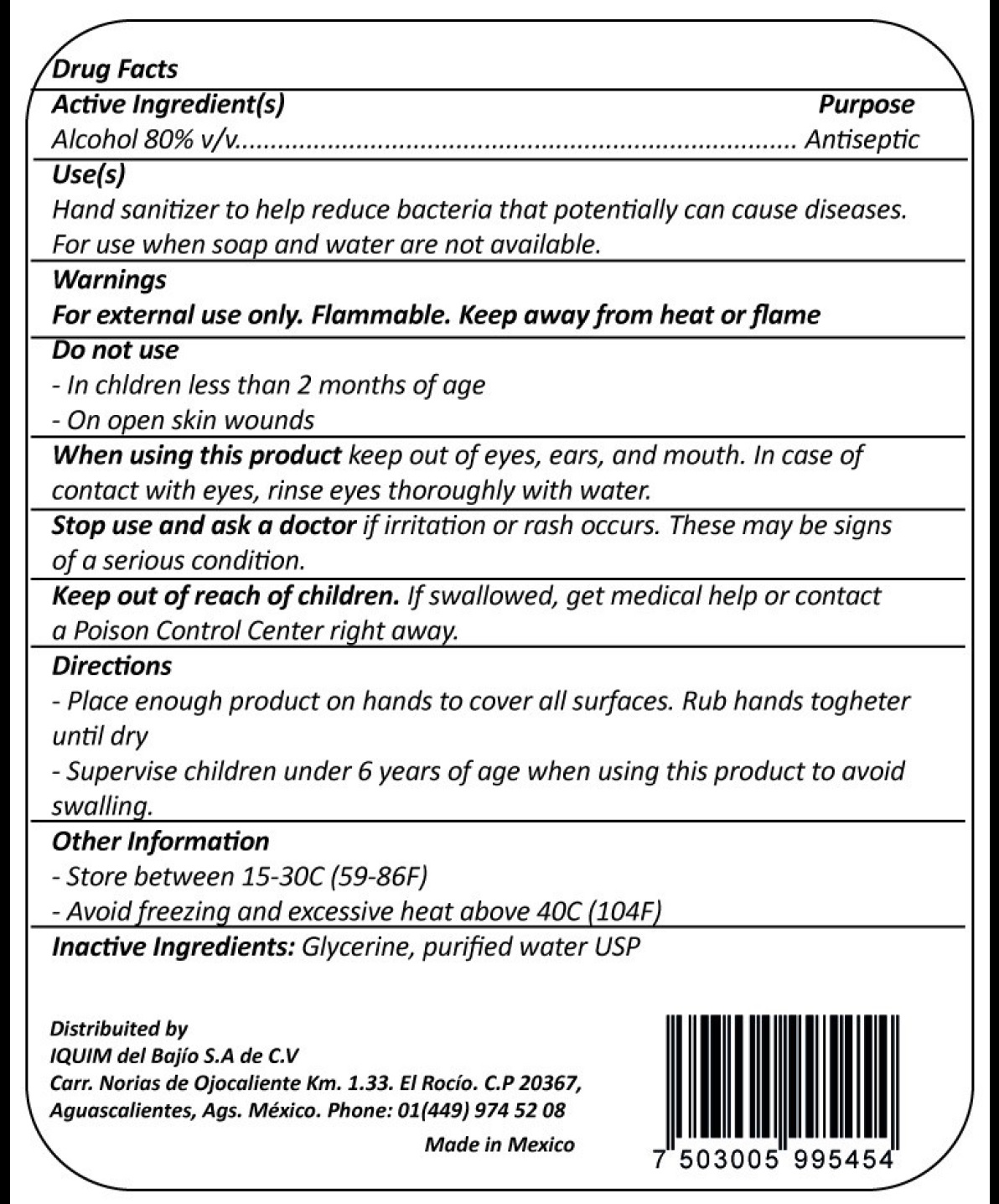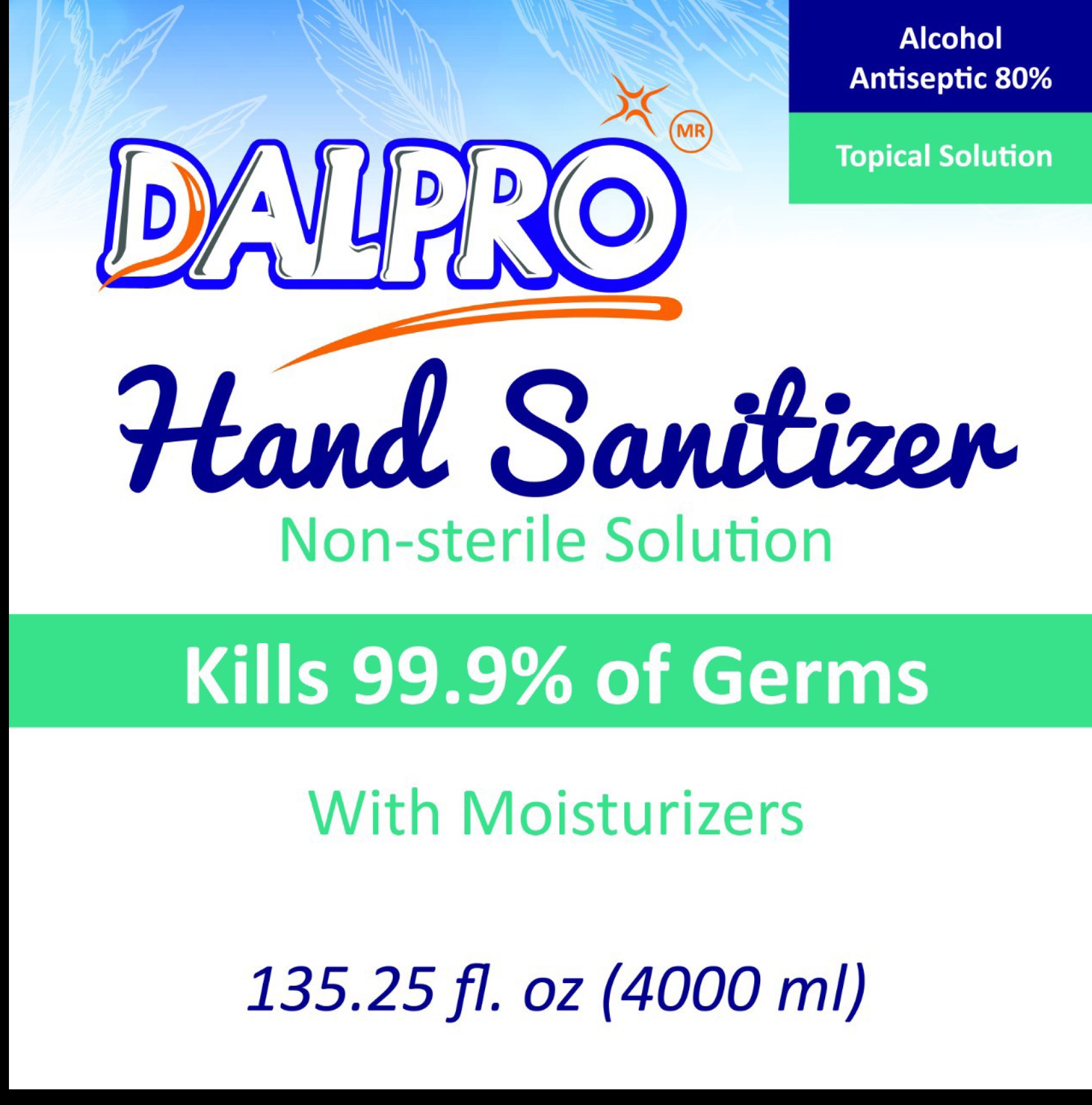 DRUG LABEL: Dalpro Hand Sanitizer Non Sterile
NDC: 79678-000 | Form: GEL
Manufacturer: Iquim del Bajio, S.A. de C.V.
Category: otc | Type: HUMAN OTC DRUG LABEL
Date: 20220223

ACTIVE INGREDIENTS: ALCOHOL 0.8 mL/1 mL
INACTIVE INGREDIENTS: GLYCERIN; WATER

Dalpro Hand Sanitizer Non Sterile

Active Ingredient(s)

Alcohol 80% v/v

Purpose

Antiseptic

Use(s)

Hand sanitizer to help reduce bacteria that potentially can cause diseases. For use when soap and water are not available.

Warnings

For external use only. Flammable. Keep away from fire or flame

Do not use

-In children less than 2 months of age

-On open skin wounds

When using this product

keep out of eyes, ears, and mouth. In case of contact with eyes, rinse eyes thoroughly with water.

Stop use and ask a doctor

if irritation or rash occurs. These may be signs of a serious condition.

Keep out of reach of children.

If swallowed, get medical help or contact a Poison Contrl Center right away.

Directions

-Place enough product on hands to cover all surfaces. Rub hands together until dry

-Supervise children under 6 years of age when using this product to avoid swallowing.

Other Information

-Store between 15-30C (59-86F)

-Avoid freezing and excessive heat above 40C (104F)

Inactive Ingredients:

Glycerin, purified water USP